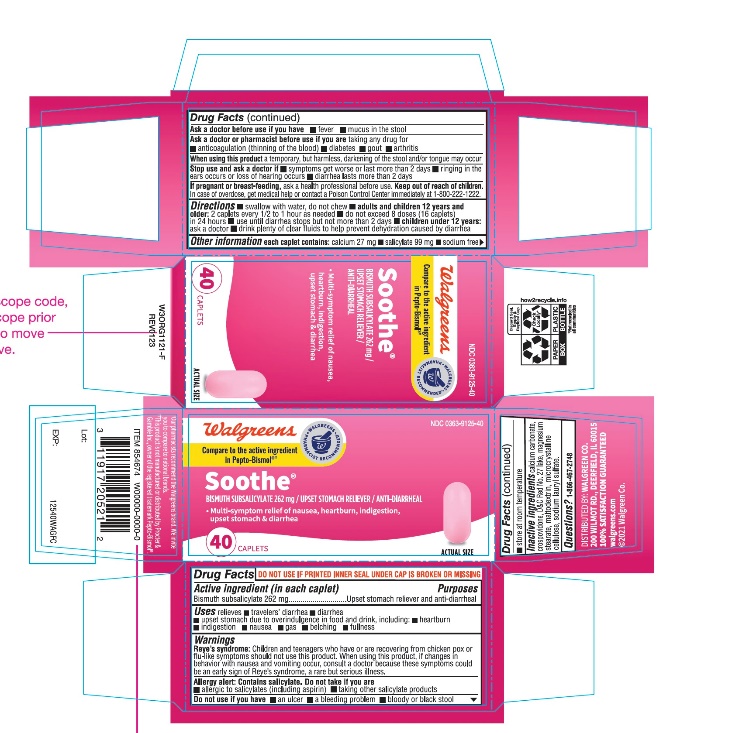 DRUG LABEL: Walgreen
NDC: 0363-9125 | Form: TABLET, FILM COATED
Manufacturer: WALGREEN CO.
Category: otc | Type: HUMAN OTC DRUG LABEL
Date: 20251125

ACTIVE INGREDIENTS: BISMUTH SUBSALICYLATE 262 mg/1 1
INACTIVE INGREDIENTS: CALCIUM CARBONATE; CROSPOVIDONE, UNSPECIFIED; D&C RED NO. 27; MAGNESIUM STEARATE; MALTODEXTRIN; MICROCRYSTALLINE CELLULOSE; SODIUM LAURYL SULFATE

Walgreen Soothe® Bismuth Subsalicylate 262 mg Caplets

Drug Facts

Active ingredient (in each caplets)

Bismuth subsalicylate 262 mg

Purpose

Upset stomach reliever/anti-diarrheal

Uses

Relieves:

- travelers’ diarrhea
- diarrhea
- upset stomach due to overindulgence in food and drink, including:
- belching
- indigestion
- gas
- fullness
- heartburn
- nausea

Warnings

Reye's syndrome:Children and teenagers who have or are recovering from chicken pox or flu-like symptoms should not use this product. When using this product, if changes in behavior with nausea and vomiting occur, consult a doctor because these symptoms could be an early sign of Reye's syndrome, a rare but serious illness.

Allergy alert: Contains salicylates.Do not take if you are:

- allergic to salicylates (including aspirin)
- taking other salicylate products

Do not use if you have

- an ulcer
- a bleeding problem
- bloody or black stool

Ask a doctor before use if you have

- fever
- mucus in the stool

Ask a doctor or pharmacist before use if you aretaking any drug for

- anticoagulation (thinning the blood)
- diabetes
- gout
- arthritis

WHEN USING

When using this producta temporary, but harmless, darkening of the stool and/or tongue may occur.

Stop use and ask a doctor if

- symptoms get worse
- ringing in the ears or loss of hearing occurs
- diarrhea lasts more than 2 days

PREGNANCY OR BREAST FEEDING

If pregnant or breast-feeding,ask a health professional before use.

Keep out of reach of children.In case of overdose, get medical help or contact a Poison Control Center right away at 1-800-222-1222.

Directions

- swallow with water; do not chew
- adults and children 12 years and over:2 caplets every 1/2 to 1 hour as needed.
  Do not exceed 8 doses (16 tablets) in 24 hours.
- use until diarrhea stops, but not more than 2 days
- children under 12 years:ask a doctor
- drink plenty of clear fluids to help prevent dehydration caused by diarrhea

Other information

- each tablet contains: calcium 27 mg, sodium 3 mg
- salicylate 99 mg
- low sodium
- sugar free
- store at room temperature

Inactive ingredients

calcium carbonate, crospovidone, D&C red # 27 aluminum lake, magnesium stearate, maltodextrin, microcrystalline cellulose, sodium lauryl sulfate.

Questions or comments?

Call 1- 866-467-2748

TAMPER EVIDENT: DO NOT USE IF PRINTED SEAL UNDER CAP IS BROKEN OR MISSING.

PACKAGE LABEL

NDC 0363-9125-40

Compare to Pepto-Bismol® active ingredient††

Soothe®

BISMUTH SUBSALICYLATE, 262 mg/

UPSET STOMACH RELIEVER / ANTI-DIARRHEAL

- Multi-symptom relief of nausea, heartburn, indigestion, upset stomach & diarrhea

40 CAPLETS.

††Walgreens Pharmacist Survey

††This product is not manufactured or distributed by Procter & Gamble, owner of the registered trademark Pepto-Bismol®

Walgreens

Trusted since 1901™

PHARMACIST RECOMMENDED

Health expertise you rely on™.

KEEP THIS CARTON FOR FUTURE REFERENCE ON FULL LABELING.

DISTRIBUTED BY: WALGREEN CO. 200 WILMOT RD., DEERFIELD, IL 60015

100% SATISFACTION GUARANTEED

walgreens.com©2021 Walgreen Co